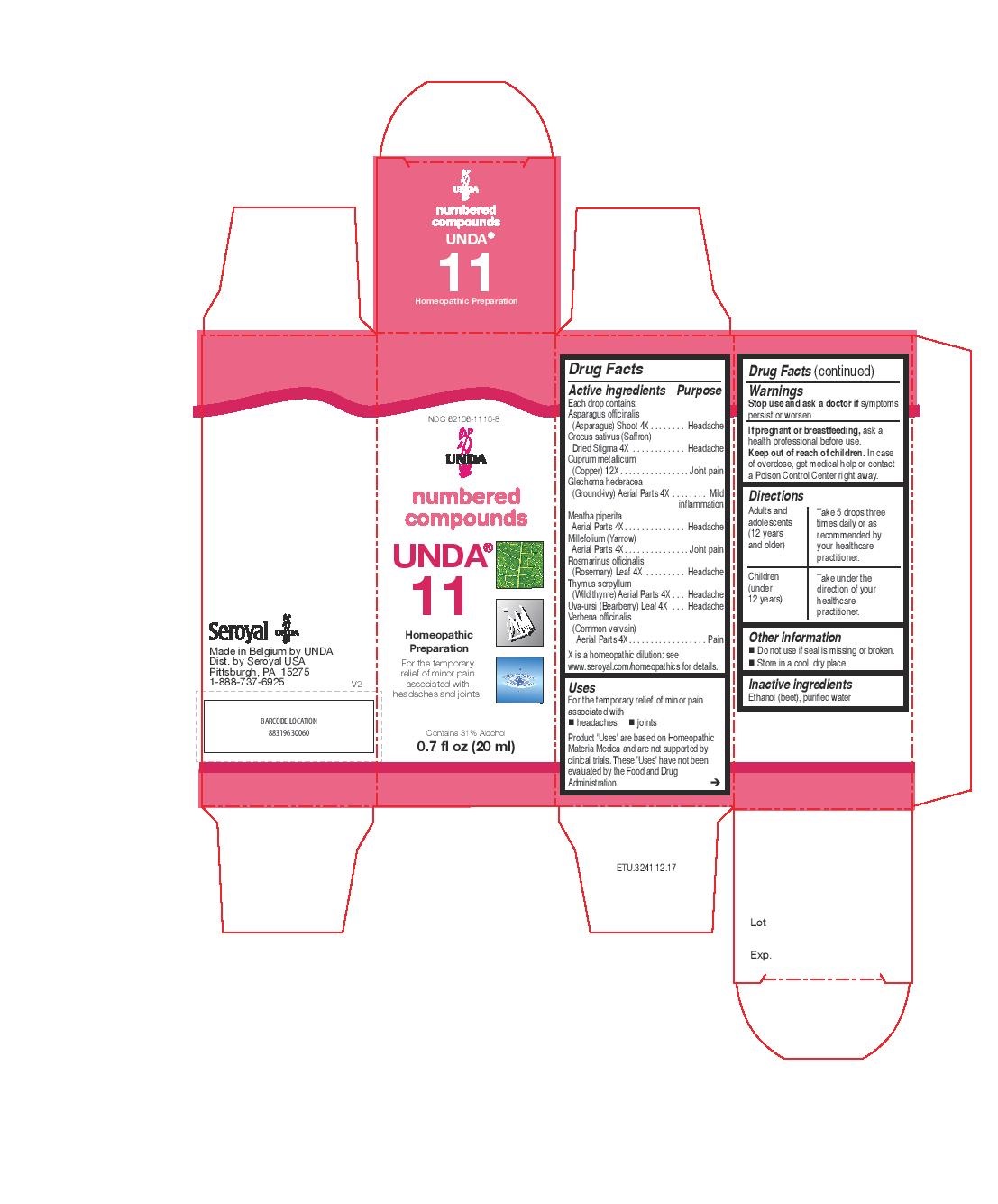 DRUG LABEL: Unda 11
NDC: 62106-1110 | Form: LIQUID
Manufacturer: Seroyal USA
Category: homeopathic | Type: HUMAN OTC DRUG LABEL
Date: 20221108

ACTIVE INGREDIENTS: VERBENA OFFICINALIS 4 [hp_X]/20 mL; COPPER 12 [hp_X]/20 mL; ASPARAGUS 4 [hp_X]/20 mL; GLECHOMA HEDERACEA 4 [hp_X]/20 mL; ARCTOSTAPHYLOS UVA-URSI LEAF 4 [hp_X]/20 mL; MENTHA PIPERITA 4 [hp_X]/20 mL; ACHILLEA MILLEFOLIUM 4 [hp_X]/20 mL; THYMUS SERPYLLUM 4 [hp_X]/20 mL; SAFFRON 4 [hp_X]/20 mL; ROSMARINUS OFFICINALIS FLOWERING TOP 4 [hp_X]/20 mL
INACTIVE INGREDIENTS: ALCOHOL; WATER

UNDA 11

Active ingredients
Each drop contains:
Asparagus officinalis (Asparagus) Shoot 4X
Crocus sativus (Saffron) Dried Stigma 4X
Cuprum metallicum (Copper) 12X
Glechoma hederacea (Ground-ivy) Aerial Parts 4X
Mentha piperita Aerial Parts 4X
Millefolium (Yarrow) Aerial Parts 4X
Rosmarinus officinalis (Rosemary) Leaf 4X
Thymus serpyllum (Wild thyme) Aerial Parts 4X
Uva-ursi (Bearberry) Leaf 4X
Verbena officinalis (Common vervain) Aerial Parts 4X

Uses

For the temporary relief of minor pain
associated with

headaches

joints

Warnings
Stop use and ask a doctor if symptoms persist or worsen.

If pregnant or breastfeeding, ask a health professional before use.

Keep out of reach of children.

In case of overdose, get medical help or contact a
Poison Control Center right away.

PREGNANCY OR BREAST FEEDING

If pregnant or breastfeeding, ask a health professional before use.

Keep out of reach of children.

OVERDOSAGE

In case of overdose, get medical help or contact a

Poison Control Center right away.

Other information
Do not use if seal is missing or broken.
Store in a cool, dry place.

Inactive ingredients
Ethanol (beet), purified water

Directions
Adults and adolescents (12 years and older)

Take 5 drops three times daily or as recommended by your healthcare practitioner.
Children (under 12 years)
Take under the direction of your healthcare practitioner.

Uses

For the temporary relief of minor pain
associated with
headaches

joints

Directions
Adults and adolescents (12 years and older)

Take 5 drops three times daily or as recommended by your healthcare practitioner.
Children (under 12 years)
Take under the direction of your healthcare practitioner.

PACKAGE LABEL

NDC 62106-1110-8

UNDA

numbered compounds

UNDA 11

Homeopathic Preparation

For the temporary relief of minor pain
associated with headaches and joints.

Contains 31% Alcohol
0.7 fl oz (20 ml)